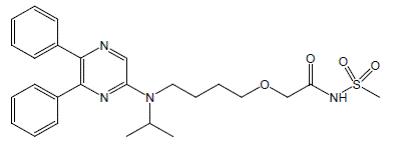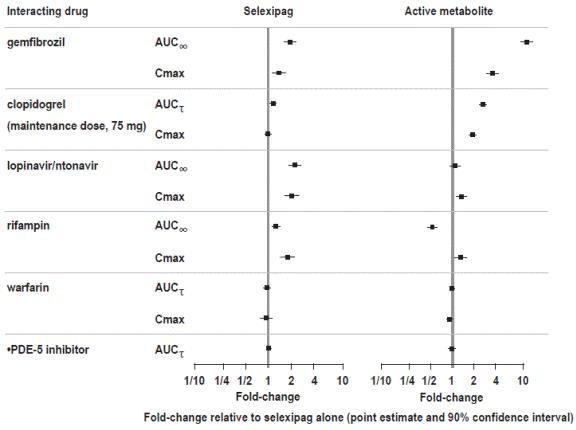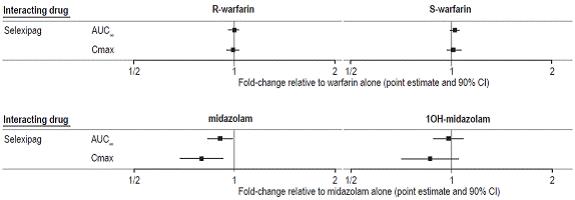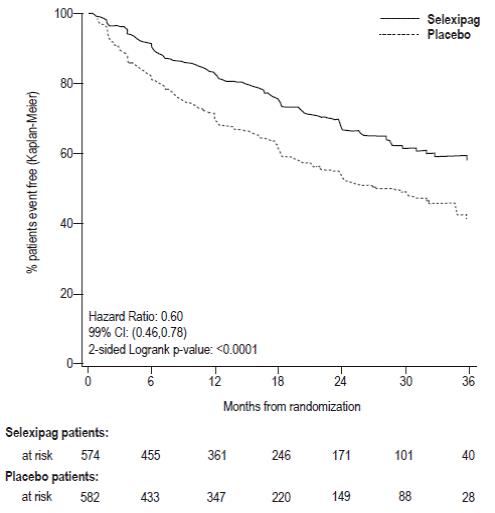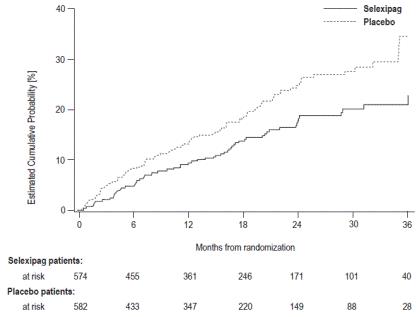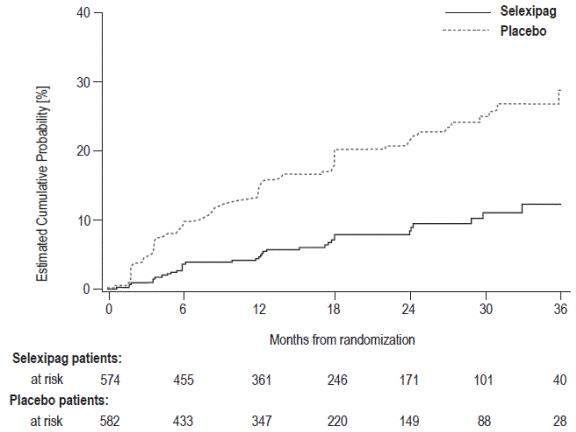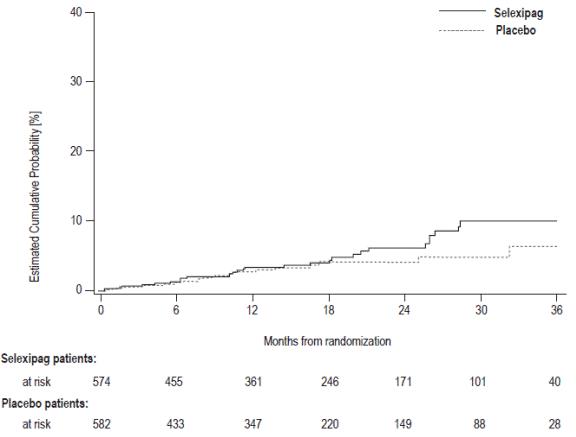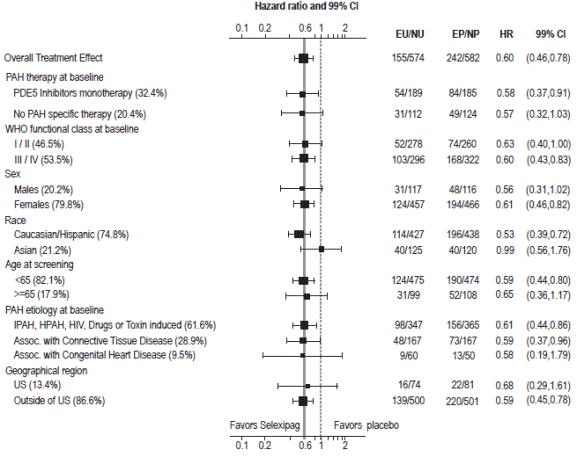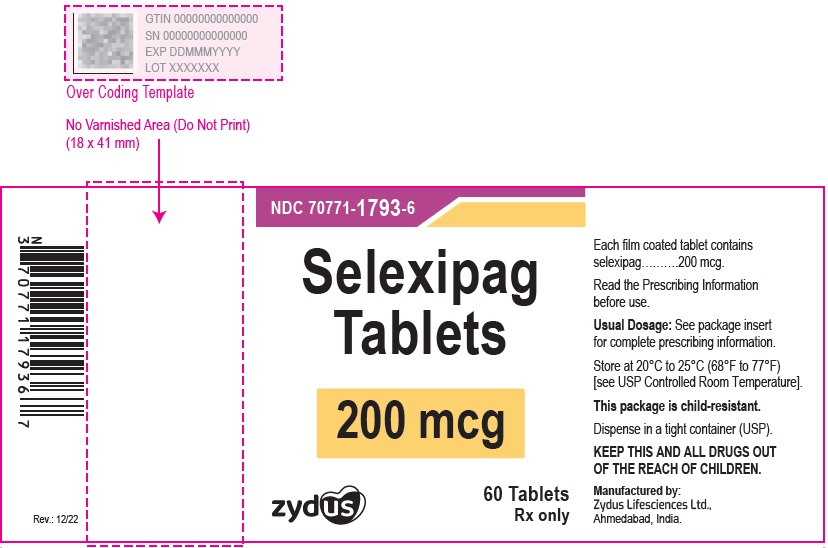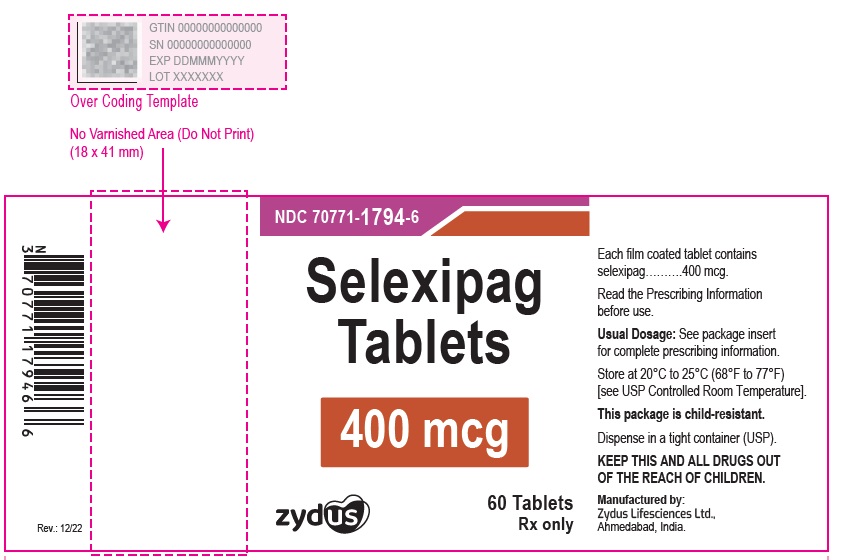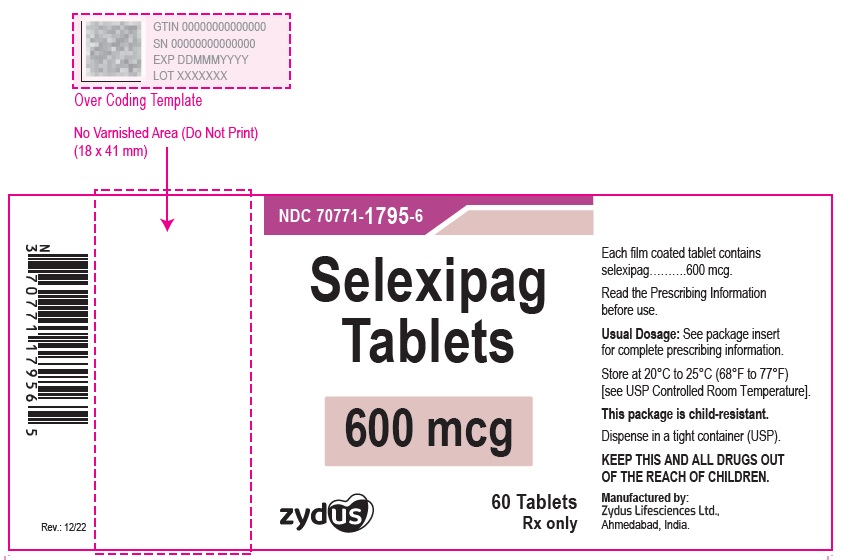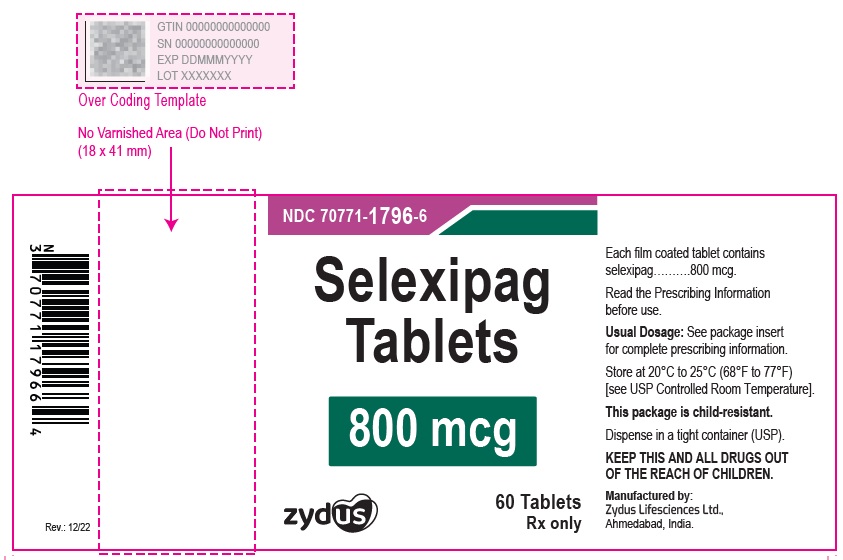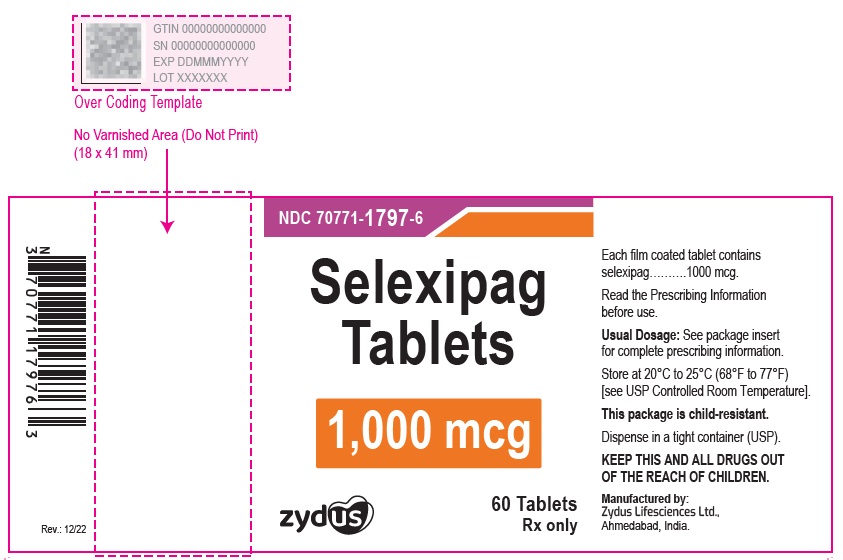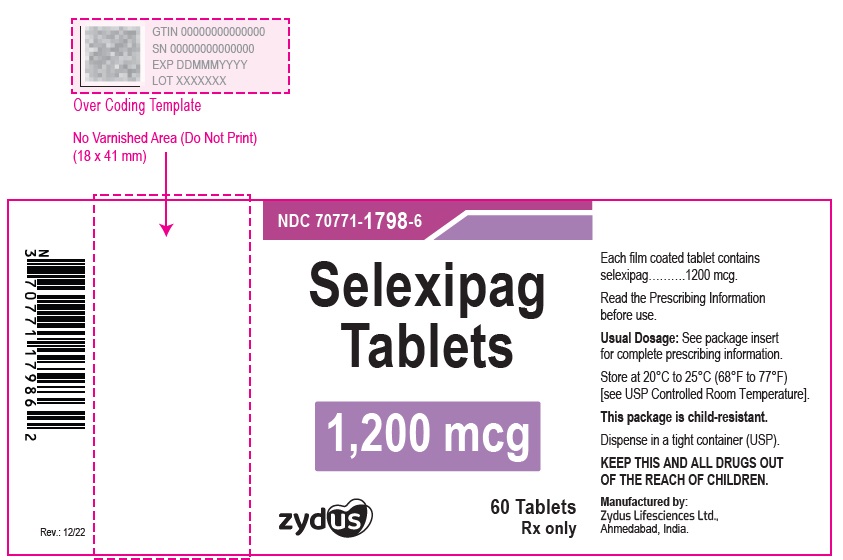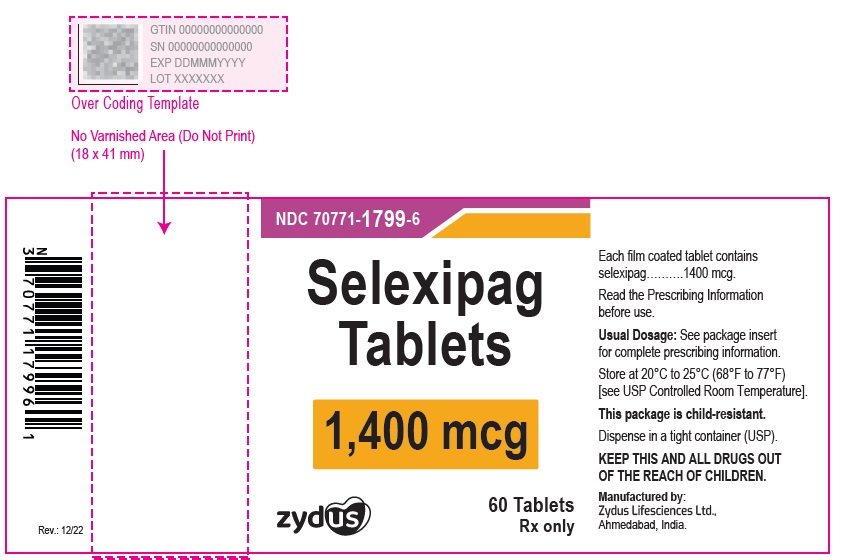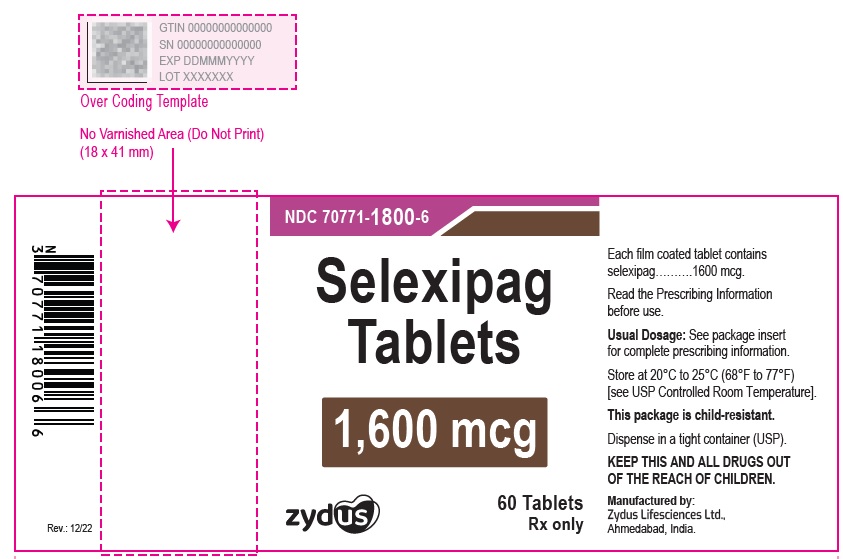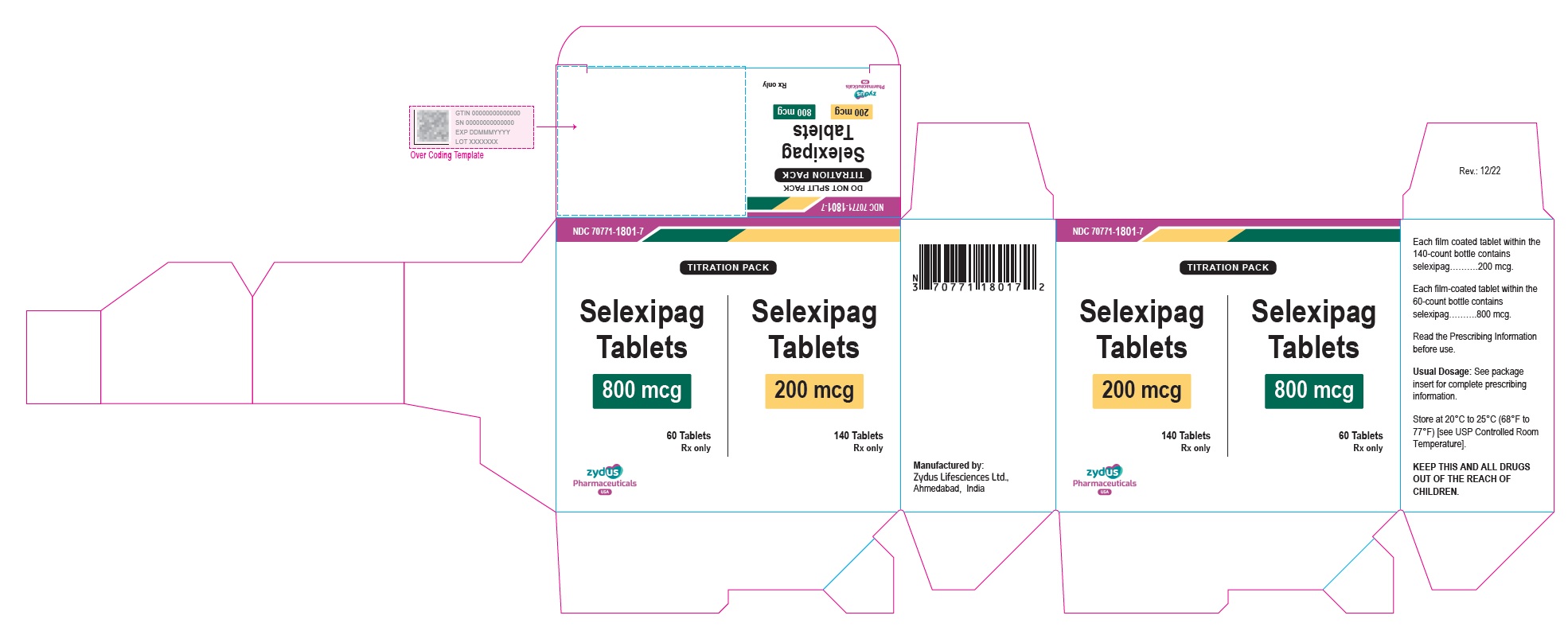 DRUG LABEL: Selexipag
NDC: 70771-1793 | Form: TABLET, FILM COATED
Manufacturer: Zydus Lifesciences Limited
Category: prescription | Type: HUMAN PRESCRIPTION DRUG LABEL
Date: 20251107

ACTIVE INGREDIENTS: SELEXIPAG 200 ug/1 1
INACTIVE INGREDIENTS: CARNAUBA WAX; CELLULOSE, MICROCRYSTALLINE; FERRIC OXIDE RED; FERRIC OXIDE YELLOW; HYDROXYPROPYL CELLULOSE (110000 WAMW); HYPROMELLOSE 2910 (6 MPA.S); LOW-SUBSTITUTED HYDROXYPROPYL CELLULOSE (11% HYDROXYPROPYL; 120000 MW); MAGNESIUM STEARATE; PROPYLENE GLYCOL; SILICON DIOXIDE; STARCH, CORN; TITANIUM DIOXIDE

HIGHLIGHTS OF PRESCRIBING INFORMATION

These highlights do not include all the information needed to use SELEXIPAG TABLETS safely and effectively. See full prescribing information for SELEXIPAG TABLETS.
SELEXIPAG tablets, for oral use
Initial U.S. Approval: 2015

RECENT MAJOR CHANGES

Contraindications (4) 10/2021

1 INDICATIONS AND USAGE

Selexipag tablets are a prostacyclin receptor agonist indicated for the treatment of pulmonary arterial hypertension (PAH, WHO Group I) to delay disease progression and reduce the risk of hospitalization for PAH. (1.1)

2 DOSAGE AND ADMINISTRATION

- Selexipag tablets starting dose: 200 mcg twice daily. (2.1)
- Increase the dose by 200 mcg twice daily at weekly intervals to the highest tolerated dose up to 1,600 mcg twice daily. (2.1)
- Maintenance dose is determined by tolerability. (2.1)
- Moderate hepatic impairment: Starting dose 200 mcg once daily , increase the dose by 200 mcg once daily at weekly intervals to the highest tolerated dose up to 1,600 mcg. (2.5)

3 DOSAGE FORMS AND STRENGTHS

Tablets: 200 mcg, 400 mcg, 600 mcg, 800 mcg, 1,000 mcg, 1,200 mcg, 1,400 mcg, 1,600 mcg.

4 CONTRAINDICATIONS

Concomitant use with strong CYP2C8 inhibitors. (4, 7.1, 12.3)

Hypersensitivity to the active substance or to any of the excipients. (4)

5 WARNINGS AND PRECAUTIONS

Pulmonary edema in patients with pulmonary veno-occlusive disease. If confirmed, discontinue treatment. (5.1)

6 ADVERSE REACTIONS

Adverse reactions occurring more frequently (≥5%) on selexipag compared to placebo are headache, diarrhea, jaw pain, nausea, myalgia, vomiting, pain in extremity, and flushing. (6.1)

To report SUSPECTED ADVERSE REACTIONS, contact Zydus Pharmaceuticals (USA) Inc. at 1-877-993-8779 or FDA at 1-800-FDA-1088 or www.fda.gov/medwatch.

7 DRUG INTERACTIONS

- Moderate CYP2C8 inhibitors (e.g., clopidogrel, deferasirox and teriflunomide) increase exposure to the active metabolite of selexipag. Reduce the dosing of selexipag to once daily (2.6, 7.1, 12.3).
- CYP2C8 inducers (e.g., rifampin) decrease exposure to the active metabolite. Increase up to twice the dose of selexipag (7.2, 12.3).

8 USE IN SPECIFIC POPULATIONS

- Nursing mothers: Discontinue selexipag or breastfeeding. (8.2)
- Severe hepatic impairment: Avoid use. (8.6)

FULL PRESCRIBING INFORMATION

1 INDICATIONS AND USAGE

1.1 Pulmonary Arterial Hypertension

Selexipag tablets are indicated for the treatment of pulmonary arterial hypertension (PAH, WHO Group I) to delay disease progression and reduce the risk of hospitalization for PAH.

Effectiveness of selexipag tablets was established in a long-term study in PAH patients with WHO Functional Class II-III symptoms.

Patients had idiopathic and heritable PAH (58%), PAH associated with connective tissue disease (29%), PAH associated with congenital heart disease with repaired shunts (10%) [see Clinical Studies (14.1)] .

2 DOSAGE AND ADMINISTRATION

2.1 Recommended Dosage

The recommended starting dosage of selexipag tablets is 200 micrograms (mcg) given twice daily. Tolerability may be improved when taken with food [see Clinical Pharmacology (12.3)].

Increase the dose in increments of 200 mcg twice daily, usually at weekly intervals, to the highest tolerated dose up to 1,600 mcg twice daily. If a patient reaches a dose that cannot be tolerated, the dose should be reduced to the previous tolerated dose.

Do not split, crush, or chew tablets.

2.4 Interruptions and Discontinuations

If a dose of selexipag tablets is missed, patients should take a missed dose as soon as possible unless the next dose is within the next 6 hours.

If treatment is missed for 3 days or more, restart selexipag tablets at a lower dose and then retitrate.

2.5 Dosage Adjustment in Patients with Hepatic Impairment

No dose adjustment of selexipag is necessary for patients with mild hepatic impairment (Child-Pugh class A).

For patients with moderate hepatic impairment (Child-Pugh class B), the starting dose of selexipag tablets is 200 mcg once daily. Increase in increments of 200 mcg once daily at weekly intervals, as tolerated [see Use in Specific Populations (8.6) and Clinical Pharmacology (12.3)].

Avoid use of selexipag in patients with severe hepatic impairment (Child-Pugh class C).

2.6 Dosage Adjustment with Co-administration of Moderate CYP2C8 Inhibitors

When co-administered with moderate CYP2C8 inhibitors (e.g., clopidogrel, deferasirox and teriflunomide), reduce the dosing of selexipag to once daily [see Drug Interactions (7.1) and Clinical Pharmacology (12.3)].

3 DOSAGE FORMS AND STRENGTHS

Selexipag tablets are available in the following strengths:

- 200 mcg [Beige colored, round, film coated tablet, debossed with "S2" on one side and plain on other side]
- 400 mcg [Pink colored, round, film coated tablet, debossed with "S4" on one side and plain on other side.]
- 600 mcg [Grey colored, round, film coated tablet, debossed with "S6" on one side and plain on other side.]
- 800 mcg [Green colored, round, film coated tablet, debossed with "S8" on one side and plain on other side.]
- 1,000 mcg [Yellow colored, round, film coated tablet, debossed with "S10" on one side and plain on other side.]
- 1,200 mcg [Dark grey colored, round, film coated tablet, debossed with "S12" on one side and plain on other side.]
- 1,400 mcg [Dark yellow colored, round, film coated tablet, debossed with "S14" on one side and plain on other side.]
- 1,600 mcg [Brown colored, round, film coated tablet, debossed with "S16" on one side and plain on other side.]

4 CONTRAINDICATIONS

Hypersensitivity to the active substance or to any of the excipients.

Concomitant use of strong inhibitors of CYP2C8 (e.g., gemfibrozil) [see Drug Interactions (7.1) and Clinical Pharmacology (12.3)].

5 WARNINGS AND PRECAUTIONS

5.1 Pulmonary Edema with Pulmonary Veno-Occlusive Disease

Should signs of pulmonary edema occur, consider the possibility of associated pulmonary veno-occlusive disease. If confirmed, discontinue selexipag.

6 ADVERSE REACTIONS

6.1 Clinical Trial Experience

Because clinical trials are conducted under widely varying conditions, adverse reaction rates observed in the clinical trials of a drug cannot be directly compared to rates in the clinical trials of another drug and may not reflect the rates observed in practice.

The safety of selexipag tablets has been evaluated in a long-term, placebo-controlled study enrolling 1,156 patients with symptomatic PAH (GRIPHON study) [see Clinical Studies (14)]. The exposure to selexipag in this trial was up to 4.2 years with median duration of exposure of 1.4 years.

Table 1 presents adverse reactions more frequent on selexipag tablets than on placebo by ≥3%.

Table 1 Adverse Reactions
Adverse Reaction | Selexipag tablets N=575 | Placebo N=577
Headache | 65% | 32%
Diarrhea | 42% | 18%
Jaw pain | 26% | 6%
Nausea | 33% | 18%
Myalgia | 16% | 6%
Vomiting | 18% | 9%
Pain in extremity | 17% | 8%
Flushing | 12% | 5%
Arthralgia | 11% | 8%
Anemia | 8% | 5%
Decreased appetite | 6% | 3%
Rash | 11% | 8%

These adverse reactions are more frequent during the dose titration phase.

Hyperthyroidism was observed in 1% (n=8) of patients on selexipag tablets and in none of the patients on placebo.

Laboratory Test Abnormalities

Hemoglobin

In a Phase 3 placebo-controlled study in patients with PAH, mean absolute changes in hemoglobin at regular visits compared to baseline ranged from −0.34 to −0.02 g/dL in the selexipag group compared to −0.05 to 0.25 g/dL in the placebo group. A decrease in hemoglobin concentration to below 10 g/dL was reported in 8.6% of patients treated with selexipag tablets and 5 % of placebo-treated patients.

Thyroid Function Tests

In a Phase 3 placebo-controlled study in patients with PAH, a reduction (up to −0.3 MU/L from a baseline median of 2.5 MU/L) in median thyroid-stimulating hormone (TSH) was observed at most visits in the selexipag group. In the placebo group, little change in median values was apparent. There were no mean changes in triiodothyronine or thyroxine in either group.

6.2 Postmarketing Experience

The following adverse reactions have been identified during post approval use of selexipag. Because these reactions are reported voluntarily from a population of uncertain size, it is not always possible to reliably estimate their frequency or establish a causal relationship to drug exposure.

Vascular disorders: Symptomatic hypotension

7 DRUG INTERACTIONS

7.1 CYP2C8 Inhibitors

Concomitant administration with gemfibrozil, a strong inhibitor of CYP2C8, doubled the exposure to selexipag and increased exposure to the active metabolite by approximately 11-fold. Concomitant administration of selexipag with strong inhibitors of CYP2C8 (e.g., gemfibrozil) is contraindicated [see Contraindications (4) and Clinical Pharmacology (12.3)].

Concomitant administration of selexipag tablets with clopidogrel, a moderate inhibitor of CYP2C8, had no relevant effect on the exposure to selexipag and increased the exposure to the active metabolite by approximately 2.7-fold [see Clinical Pharmacology (12.3)]. Reduce the dosing of selexipag to once daily in patients on a moderate CYP2C8 inhibitor [see Dosage and Administration (2.6)].

7.2 CYP2C8 Inducers

Concomitant administration with an inducer of CYP2C8 and UGT 1A3 and 2B7 enzymes (rifampin) halved exposure to the active metabolite. Increase dose up to twice of selexipag when co-administered with rifampin. Reduce selexipag when rifampin is stopped [see Clinical Pharmacology (12.3)].

8 USE IN SPECIFIC POPULATIONS

8.1 Pregnancy

Risk Summary

There are no adequate and well-controlled studies with selexipag in pregnant women. Animal reproduction studies performed with selexipag showed no clinically relevant effects on embryofetal development and survival. A slight reduction in maternal as well as in fetal body weight was observed when pregnant rats were administered selexipag during organogenesis at a dose producing an exposure to the active metabolite approximately 47 times that in humans at the maximum recommended human dose. No adverse developmental outcomes were observed with oral administration of selexipag to pregnant rabbits during organogenesis at exposures to the active metabolite up to 50 times the human exposure at the maximum recommended human dose.

The estimated background risk of major birth defects and miscarriage for the indicated population is unknown. In the U.S. general population, the estimated background risk of major birth defects and miscarriage in clinically recognized pregnancies is 2 to 4% and 15 to 20%, respectively.

Data

Animal Data

Pregnant rats were treated with selexipag using oral doses of 2 mg/kg/day, 6 mg/kg/day, and 20 mg/kg/day (up to 47 times the exposure to the active metabolite at the maximum recommended human oral dose of 1,600 mcg twice daily on an area under the curve [AUC] basis) during the period of organogenesis (gestation days 7 to 17). Selexipag did not cause adverse developmental effects to the fetus in this study. A slight reduction in fetal body weight was observed in parallel with a slight reduction in maternal body weight at the high dose.

Pregnant rabbits were treated with selexipag using oral doses of 3 mg/kg, 10 mg/kg, and 30 mg/kg (up to 50 times the exposure to the active metabolite at the maximum recommended human oral dose of 1,600 mcg twice daily on an AUC basis) during the period of organogenesis (gestation days 6 to 18). Selexipag did not cause adverse developmental effects to the fetus in this study.

In a pre-and post-natal development study, pregnant rats were treated with selexipag from gestation day 7 through lactation day 20 at oral doses of 2, 6, and 20 mg/kg/day (up to 35 times the exposure to the active metabolite at the maximum recommended human dose of 1,600 mcg twice daily on an AUC basis). Treatment with selexipag did not cause adverse developmental effects in this study at any dose.

8.2 Lactation

It is not known if selexipag is present in human milk. Selexipag or its metabolites were present in the milk of rats. Because many drugs are present in the human milk and because of the potential for serious adverse reactions in nursing infants, discontinue nursing or discontinue selexipag.

8.4 Pediatric Use

Safety and effectiveness in pediatric patients have not been established.

8.5 Geriatric Use

Of the 1,368 subjects in clinical studies of selexipag tablets, 248 subjects were 65 years of age and older, while 19 were 75 and older. No overall differences were observed between these subjects and younger subjects, and other reported clinical experience has not identified differences in responses between the elderly and younger patients, but greater sensitivity cannot be ruled out.

8.6 Patients with Hepatic Impairment

No adjustment to the dosing regimen is needed in patients with mild hepatic impairment (Child-Pugh class A).

A once-daily regimen is recommended in patients with moderate hepatic impairment (Child-Pugh class B) due to the increased exposure to selexipag and its active metabolite. There is no experience with selexipag in patients with severe hepatic impairment (Child-Pugh class C). Avoid use of selexipag in patients with severe hepatic impairment [see Dosage and Administration (2.5) and Clinical Pharmacology (12.3)].

8.7 Patients with Renal Impairment

No adjustment to the dosing regimen is needed in patients with estimated glomerular filtration rate >15 mL/min/1.73 m^2.

There is no clinical experience with selexipag in patients undergoing dialysis or in patients with glomerular filtration rates < 15 mL/min/1.73 m^2 [see Clinical Pharmacology (12.3)].

10 OVERDOSAGE

Isolated cases of overdose with selexipag tablets up to 3,200 mcg were reported. Mild, transient nausea was the only reported consequence. In the event of overdose, supportive measures must be taken as required. Dialysis is unlikely to be effective because selexipag and its active metabolite are highly protein-bound.

11 DESCRIPTION

Selexipag tablets contains selexipag, a prostacyclin receptor agonist. The chemical name of selexipag is 2-{4-[(5,6-diphenylpyrazin-2-yl)(isopropyl)amino]butoxy}-N(methylsulfonyl) acetamide. It has a molecular formula of C26H32N4O4S and a molecular weight of 496.62. Selexipag has the following structural formula:

Selexipag is an off white to pale yellow crystalline powder that is practically insoluble in water. In the solid state selexipag is very stable, is not hygroscopic, and is not light sensitive.

Depending on the dose strength, each round film-coated tablet for oral administration contains 200 mcg, 400 mcg, 600 mcg, 800 mcg, 1,000 mcg, 1,200 mcg, 1,400 mcg, or 1,600 mcg of selexipag. The tablets include the following inactive ingredients: corn starch, colloidal silicon dioxide, hydroxypropyl cellulose, low substituted hydroxypropyl cellulose, microcrystalline cellulose and magnesium stearate. The tablets are film coated with a coating material containing hypromellose, propylene glycol, carnauba wax, titanium dioxide, along with mixtures of ferrosoferric oxide, iron oxide red or iron oxide yellow.

12 CLINICAL PHARMACOLOGY

12.1 Mechanism of Action

Selexipag is a prostacyclin receptor (IP receptor) agonist that is structurally distinct from prostacyclin. Selexipag is hydrolyzed by carboxylesterase 1 to yield its active metabolite, which is approximately 37-fold as potent as selexipag. Selexipag and the active metabolite are selective for the IP receptor versus other prostanoid receptors (EP1 to 4, DP, FP, and TP).

12.2 Pharmacodynamics

Cardiac Electrophysiology:

At the maximum tolerated dose of 1,600 mcg selexipag tablets twice daily, selexipag does not prolong the QT interval to any clinically relevant extent.

Platelet Aggregation:

Both selexipag and its active metabolite caused concentration-dependent inhibition of platelet aggregation in vitro with an IC50 of 5.5 μM and 0.21 μM, respectively. However, at clinically relevant concentrations, there was no effect on platelet aggregation test parameters as seen following multiple-dose administrations of selexipag tablets in healthy subjects from 400 mcg up to 1,800 mcg twice daily.

Pulmonary Hemodynamics:

A Phase 2 clinical study assessed hemodynamic variables after 17 weeks of oral treatment in patients with PAH WHO Functional Class II–III and concomitantly receiving another PAH therapy and/or phosphodiesterase type 5 (PDE-5) inhibitors. Patients titrating selexipag tablets to an individually tolerated dose (200 mcg twice daily increments up to 800 mcg twice daily) (N=33) achieved a statistically-significant mean reduction in pulmonary vascular resistance of 30.3% (95% confidence interval [CI] −44.7%, −12.2%) and an increase in cardiac index (median treatment effect) of 0.41 L/min/m^2 (95% CI 0.10, 0.71) compared to placebo (N=10).

Drug Interaction:

In a study in healthy subjects, selexipag tablets (400 mcg twice a day) did not influence the pharmacodynamic effect of warfarin on the international normalized ratio.

12.3 Pharmacokinetics

The pharmacokinetics of selexipag and its active metabolite have been studied primarily in healthy subjects. The pharmacokinetics of selexipag and the active metabolite, after both single-and multiple-dose oral administration, were dose-proportional up to a single dose of 800 mcg and multiple doses of up to 1,800 mcg twice daily.

In healthy subjects, inter-subject variability in exposure (area under the curve over a dosing interval, AUC) at steady-state following oral administration was 43% and 39% for selexipag and the active metabolite, respectively. Intra-subject variability in exposure was 24% and 19% for selexipag and the active metabolite, respectively.

Exposures to selexipag and the active metabolite at steady-state in PAH patients and healthy subjects were similar. The pharmacokinetics of selexipag and the active metabolite in PAH patients were not influenced by the severity of the disease and did not change with time.

The corresponding selexipag tablets and selexipag for injection doses provide similar exposure to the active metabolite in PAH patients at steady-state, whereas the exposure to selexipag is approximately twice as high after intravenous administration compared to oral administration.

Both in healthy subjects and PAH patients, after oral administration, exposure at steady-state to the active metabolite is approximately 3-to 4-fold that of selexipag.

Absorption

The absolute bioavailability of orally administered selexipag is approximately 49%. Upon oral administration, maximum observed plasma concentrations of selexipag and its active metabolite are reached within about 1 to 3 hours and 3 to 4 hours, respectively.

In the presence of food, the absorption of selexipag was prolonged resulting in a delayed time to peak concentration (Tmax) and ~30% lower peak plasma concentration (Cmax). The exposure to selexipag and the active metabolite (AUC) did not significantly change in the presence of food.

Distribution

The volume of distribution of selexipag at steady-state is 11.7 L.

Selexipag and its active metabolite are highly bound to plasma proteins (approximately 99% in total and to the same extent to albumin and alpha1-acid glycoprotein).

Metabolism

Selexipag is hydrolyzed to its active metabolite, (free carboxylic acid) in the liver and intestine by carboxylesterases. Oxidative metabolism, catalyzed mainly by CYP2C8 and to a smaller extent by CYP3A4, leads to the formation of hydroxylated and dealkylated products. UGT1A3 and UGT2B7 are involved in the glucuronidation of the active metabolite. Except for the active metabolite, none of the circulating metabolites in human plasma exceeds 3% of the total drug-related material.

Elimination

Elimination of selexipag is predominately via metabolism with a mean terminal half-life of 0.8 to 2.5 hours. The terminal half-life of the active metabolite is 6.2 to 13.5 hours. Selexipag does not accumulate following twice daily repeat administration. There is minimal accumulation of the active metabolite upon twice daily repeat administration suggesting that the effective half-life is in the range of 3 to 4 hours. The total body clearance of selexipag is 17.9 L/hour.

Excretion

In a study in healthy subjects with radiolabeled selexipag, approximately 93% of radioactive drug material was eliminated in feces and only 12% in urine. Neither selexipag nor its active metabolite were found in urine.

Specific Populations

No clinically relevant effects of sex, race, age or body weight on the pharmacokinetics of selexipag and its active metabolite have been observed in healthy subjects or PAH patients.

Age

The pharmacokinetic variables (Cmax and AUC) were similar in adult and elderly subjects up to 75 years of age. There was no effect of age on the pharmacokinetics of selexipag and the active metabolite in PAH patients.

Hepatic Impairment

In subjects with mild (Child-Pugh class A) or moderate (Child-Pugh class B) hepatic impairment, exposure to selexipag was 2-and 4-fold that seen in healthy subjects. Exposure to the active metabolite of selexipag remained almost unchanged in subjects with mild hepatic impairment and was doubled in subjects with moderate hepatic impairment [see Use in Specific Populations (8.6)].

Based on pharmacokinetic modeling of data from a study in subjects with hepatic impairment, the exposure to the active metabolite at steady-state in subjects with moderate hepatic impairment (Child-Pugh class B) after a once daily regimen is expected to be similar to that in healthy subjects receiving a twice daily regimen. The exposure to selexipag at steady-state in these patients during a once daily regimen is predicted to be approximately 2-fold that seen in healthy subjects receiving a twice-daily regimen.

Renal Impairment

A 40 to 70% increase in exposure (maximum plasma concentration and area under the plasma concentration-time curve) to selexipag and its active metabolite was observed in subjects with severe renal impairment (estimated glomerular filtration rate ≥15 mL/min/1.73 m^2and <30 mL/min/1.73 m^2) [see Use in Specific Populations (8.7)].

Drug Interaction Studies

Drug interaction studies have been performed in adult subjects using selexipag tablets.

In Vitro Studies

Selexipag is hydrolyzed to its active metabolite by carboxylesterases. Selexipag and its active metabolite both undergo oxidative metabolism mainly by CYP2C8 and to a smaller extent by CYP3A4. The glucuronidation of the active metabolite is catalyzed by UGT1A3 and UGT2B7. Selexipag and its active metabolite are substrates of OATP1B1 and OATP1B3. Selexipag is a substrate of P-gp, and the active metabolite is a substrate of the transporter of breast cancer resistance protein (BCRP).

Selexipag and its active metabolite do not inhibit or induce cytochrome P450 enzymes and transport proteins at clinically relevant concentrations.

The results of in vivo drug interaction studies are presented in Figure 1 and 2.

Figure 1 Effect of Other Drugs on Selexipag and its Active Metabolite

*PDE-5 inhibitor data from GRIPHON.

Figure 2 Effect of Selexipag on Other Drugs

13 NONCLINICAL TOXICOLOGY

13.1 Carcinogenesis, Mutagenesis, Impairment of Fertility

Carcinogenesis: In the 2-year carcinogenicity studies, chronic oral administration of selexipag revealed no evidence of carcinogenic potential in rats at 100 mg/kg/day and mice at 500 mg/kg/day which resulted in the exposures to the active metabolite more than 25 times the human exposure at the maximum recommended human oral dose of 1,600 mcg twice daily on an AUC basis.

Mutagenesis: Selexipag and the active metabolite are not genotoxic on the basis of the overall evidence of conducted genotoxicity studies.

Fertility: In rats administered with selexipag orally, the no effect dose for effects on fertility was 60 mg/kg/day which resulted in the exposure to the active metabolite approximately 175 times the human exposure at the maximum recommended human oral dose of 1,600 mcg twice daily on an AUC basis.

14 CLINICAL STUDIES

14.1 Efficacy of Selexipag Tablets in Patients with Pulmonary Arterial Hypertension

The effect of selexipag tablets on progression of PAH was demonstrated in a multi-center, double-blind, placebo-controlled, parallel group, event-driven study (GRIPHON) in 1,156 patients with symptomatic (WHO Functional Class I [0.8%], II [46%], III [53%], and IV [1%]) PAH. Patients were randomized to either placebo (N = 582), or selexipag tablets (N = 574). The dose was increased in weekly intervals by increments of 200 mcg twice a day to the highest tolerated dose up to 1,600 mcg twice a day.

The primary study endpoint was the time to first occurrence up to end-of-treatment of: a) death, b) hospitalization for PAH, c) PAH worsening resulting in need for lung transplantation, or balloon atrial septostomy, d) initiation of parenteral prostanoid therapy or chronic oxygen therapy, or e) other disease progression based on a 15% decrease from baseline in 6MWD plus worsening of Functional Class or need for additional PAH-specific therapy.

The mean age was 48 years, the majority of patients were white (65%) and female (80%). Nearly all patients were in WHO Functional Class II and III at baseline.

Idiopathic or heritable PAH was the most common etiology in the study population (58%) followed by PAH associated with connective tissue disease (29%), PAH associated with congenital heart disease with repaired shunts (10%), drugs and toxins (2%), and HIV (1%).

At baseline, the majority of enrolled patients (80%) were being treated with a stable dose of another PAH therapy (15%), PDE-5 inhibitor (32%), or both (33%).

Patients on selexipag tablets achieved doses within the following groups: 200 to 400 mcg (23%), 600 to 1,000 mcg (31%) and 1,200 to 1,600 mcg (43%).

Treatment with selexipag tablets resulted in a 40% reduction (99% CI: 22 to 54%; two-sided log-rank p-value < 0.0001) of the occurrence of primary endpoint events compared to placebo (Table 2; Figure 3). The beneficial effect of selexipag was primarily attributable to a reduction in hospitalization for PAH and a reduction in other disease progression events (Table 2). The observed benefit of selexipag was similar regardless of the dose achieved when patients were titrated to their highest tolerated dose [see Dosage and Administration (2.1)].

Figure 3 Kaplan-Meier Estimates of the First Morbidity-Mortality Event in GRIPHON

Table 2 Primary Endpoints and Related Components in GRIPHON

 | Selexipag N=574 |  | Placebo N=582 |  | Hazard Ratio (99% CI) | p-value
 | n | % | n | %
Primary endpoint events up to the end of treatment
All primary endpoint events As first event: | 155 | 27.0 | 242 | 41.6 | 0.60 [0.46,0.78] | <0.0001
• Hospitalization for PAH • Other disease progression (Decrease in 6MWD plus worsening functional class or need for other therapy) • Death | 78 38 | 13.6 6.6 | 109 100 | 18.7 17.2
• Hospitalization for PAH • Other disease progression (Decrease in 6MWD plus worsening functional class or need for other therapy) • Death | 28 | 4.9 | 18 | 3.1
• Parenteral prostanoid or chronic oxygen therapy • PAH worsening resulting in need for lung transplantation or balloon atrial septostomy | 10 1 | 1.7 0.2 | 13 2 | 2.2 0.3

It is not known if the excess number of deaths in the selexipag group is drug-related because there were so few deaths and the imbalance was not observed until 18 months into GRIPHON.

Figures 4A, B, and C show time to first event analyses for primary endpoint components of hospitalization for PAH (A), other disease progression (B), and death (C) all censored 7 days after any primary end point event (because many patients on placebo transitioned to open-label selexipag at this point).

Figure 4A Hospitalization for PAH as the First Endpoint in GRIPHON

Figure 4B Disease Progression as the First Endpoint in GRIPHON

Figure 4C Death as the First Endpoint in GRIPHON

The treatment effect of selexipag on time to first primary event was consistent irrespective of background PAH therapy (i.e. in combination with another PAH therapy, PDE-5i, both, or without background therapy) (Figure 5).

Figure 5 Subgroup Analyses of the Primary Endpoint in GRIPHON

Note: Race group "Other" is not displayed in analysis, as the population is less than 30. EU = Number of selexipag patients with events, NU = Number of patients randomized to selexipag, EP = Number of Placebo patients with events, NP = Number of patients randomized to Placebo, HR = Hazard Ratio, CI = Confidence Interval, the size of the squares represent the number of patients in the subgroup.

Note: The figure above presents effects in various subgroups all of which are baseline characteristics and all were pre-specified. The 99% confidence limits that are shown do not take into account how many comparisons were made, nor do they reflect the effect of a particular factor after adjustment for all other factors. Apparent homogeneity or heterogeneity among groups should not be over-interpreted.

6-Minute Walk Distance (6MWD)

Exercise capacity was evaluated as a secondary endpoint. Median absolute change from baseline to week 26 in 6MWD measured at trough (i.e., at approximately 12 hours post-dose) was +4 meters with selexipag and -9 meters in the placebo group. This resulted in a placebo-corrected median treatment effect of 12 meters (99% CI: 1, 24 meters; two-sided p = 0.005).

Long-Term Treatment of PAH

In long-term follow-up of patients who were treated with selexipag in the pivotal study and the open-label extension (N=574), Kaplan-Meier estimates of survival of these patients across the GRIPHON study and the long-term extension study at 1, 2, 5 and 7 years were 92%, 85%, 71%, and 63%, respectively. The median exposure to selexipag was 3 years. These uncontrolled observations do not allow comparison with a control group not given selexipag and cannot be used to determine the long-term effect of selexipag on mortality.

16 HOW SUPPLIED/STORAGE AND HANDLING

Selexipag tablets, 200 mcg are beige colored, round, film coated tablet, debossed with "S2" on one side and plain on other side and are supplied as follows:

NDC 70771-1793-6 in bottles of 60 tablets with child-resistant closure

NDC 70771-1793-8 in bottles of 140 tablets with child-resistant closure

Selexipag tablets, 400 mcg are pink colored, round, film coated tablet, debossed with "S4" on one side and plain on other side and are supplied as follows:

NDC 70771-1794-6 in bottles of 60 tablets with child-resistant closure

Selexipag tablets, 600 mcg are grey colored, round, film coated tablet, debossed with "S6" on one side and plain on other side and are supplied as follows:

NDC 70771-1795-6 in bottles of 60 tablets with child-resistant closure

Selexipag tablets, 800 mcg are green colored, round, film coated tablet, debossed with "S8" on one side and plain on other side and are supplied as follows:

NDC 70771-1796-6 in bottles of 60 tablets with child-resistant closure

Selexipag tablets, 1,000 mcg are yellow colored, round, film coated tablet, debossed with "S10" on one side and plain on other side and are supplied as follows:

NDC 70771-1797-6 in bottles of 60 tablets with child-resistant closure

Selexipag tablets, 1,200 mcg are dark grey colored, round, film coated tablet, debossed with "S12" on one side and plain on other side and are supplied as follows:

NDC 70771-1798-6 in bottles of 60 tablets with child-resistant closure

Selexipag tablets, 1,400 mcg are dark yellow colored, round, film coated tablet, debossed with "S14" on one side and plain on other side and are supplied as follows:

NDC 70771-1799-6 in bottles of 60 tablets with child-resistant closure

Selexipag tablets, 1,600 mcg are brown colored, round, film coated tablet, debossed with "S16" on one side and plain on other side and are supplied as follows:

NDC 70771-1800-6 in bottles of 60 tablets with child-resistant closure

Selexipag tablets are also supplied in a Titration Pack [NDC 70771-1801-7] that includes a 140-count bottle of 200-mcg tablets and a 60-count bottle of 800-mcg tablets.

Store at 20ºC to 25ºC (68ºF to 77ºF) [see USP Controlled Room Temperature].

Keep this and all drugs out of the reach of children.

17 PATIENT COUNSELING INFORMATION

Advise the patient to read the FDA-approved patient labeling (Patient Information).

Inform Patients:

- To take a missed dose as soon as possible, unless the next dose is within the next 6 hours.
- Not to split, crush, or chew tablets.

Manufactured by:

Zydus Lifesciences Ltd.

Ahmedabad, India

Rev.: 09/22

PATIENT INFORMATION
Selexipag (se lex' i pag) tablets

What is selexipag tablets?

- Selexipag tablets are a prescription medicine used to treat pulmonary arterial hypertension (PAH) which is high blood pressure in the arteries of your lungs.
- Selexipag tablets can help slow down the progression of your disease and lower your risk of being hospitalized for PAH.

It is not known if selexipag tablets are safe and effective in children.

Do not take selexipag tablets if you

- take gemfibrozil because this medicine may affect how selexipag tablets work and cause side effects.
- are allergic to selexipag or any of the other ingredients of this medicine (listed under Inactive ingredients).

Before you take selexipag tablets, tell your healthcare provider about all of your medical conditions, including if you:

- have liver problems.
- have narrowing of the pulmonary veins, a condition called pulmonary veno-occlusive disease.
- are pregnant or plan to become pregnant. It is not known if selexipag tablets will harm your unborn baby.
- are breastfeeding or plan to breastfeed. It is not known if selexipag passes into your breast milk. You and your healthcare provider should decide if you will take selexipag tablets or breastfeed. You should not do both.

Tell your healthcare provider about all the medicines you take, including prescription and over-the-counter medicines, vitamins, and herbal supplements. Selexipag tablets and other medicines may affect each other causing side effects. Do not start any new medicine until you check with your healthcare provider.

How should I take selexipag tablets?

- Take selexipag tablets exactly as your healthcare provider tells you to take it. Do not stop taking selexipag tablets unless your healthcare provider tells you to stop.
- Your healthcare provider will slowly increase your dose to find the dose of selexipag tablets that is right for you.
- If you have side effects, your healthcare provider may tell you to change your dose of selexipag tablets.
- Selexipag tablets can be taken with or without food. Taking selexipag tablets with food may help you tolerate selexipag tablets better.
- Selexipag tablets are usually taken 2 times each day.
- Swallow selexipag tablets whole. Do not split, crush or chew selexipag tablets.
- If you miss a dose of selexipag tablets, take it as soon as you remember. If your next scheduled dose is due within 6 hours, skip the missed dose. Take the next dose at your regular time.
- If you miss 3 or more days of selexipag tablets, call your healthcare provider to see if your dose needs to be changed.
- If you take too much selexipag tablets, call your healthcare provider or go to the nearest hospital emergency room right away.

What are the possible side effects of selexipag tablets?
The most common side effects of selexipag tablets include:

- headache
- jaw pain
- muscle pain
- pain in arms or legs
- pain in joints
- decreased appetite

- diarrhea
- nausea
- vomiting
- flushing
- low red blood cell count
- rash

These are not all of the possible side effects of selexipag tablets.

Call your doctor for medical advice about side effects. You may report side effects to FDA at 1-800-FDA-1088.

How should I store selexipag tablets?

- Store selexipag tablets at room temperature between 68°F and 77°F (20°C and 25°C).

Keep selexipag tablets and all medicines out of the reach of children.

General information about the safe and effective use of selexipag tablets
Medicines are sometimes prescribed for purposes other than those listed in a Patient Information leaflet.
Do not use selexipag tablets for a condition for which it was not prescribed. Do not give selexipag tablets to other people, even if they have the same symptoms that you have. It may harm them. You can ask your healthcare provider or pharmacist for information about selexipag tablets that is written for health professionals.

What are the ingredients in selexipag tablets?
Active ingredient: selexipag
Inactive ingredients: corn starch, colloidal silicon dioxide, hydroxypropyl cellulose, low substituted hydroxypropyl cellulose, microcrystalline cellulose and magnesium stearate. The tablets are film coated with a coating material containing hypromellose, propylene glycol, carnauba wax, titanium dioxide, along with mixtures of ferrosoferric oxide, iron oxide red or iron oxide yellow.
Manufactured by:
Zydus Lifesciences Ltd.
Ahmedabad, India
For more information, call 1-877-993-8779.

The Patient Information has been approved by the U.S. Food and Drug Administration.

Revised: 09/2022

PACKAGE LABEL.PRINCIPAL DISPLAY PANEL

NDC 70771-1793-6

Selexipag Tablets

200 mcg

60 Tablets

Rx only

NDC 70771-1794-6

Selexipag Tablets

400 mcg

60 Tablets

Rx only

NDC 70771-1795-6

Selexipag Tablets

600 mcg

60 Tablets

Rx only

NDC 70771-1796-6

Selexipag Tablets

800 mcg

60 Tablets

Rx only

NDC 70771-1797-6

Selexipag Tablets

1,000 mcg

60 Tablets

Rx only

NDC 70771-1798-6

Selexipag Tablets

1,200 mcg

60 Tablets

Rx only

NDC 70771-1799-6

Selexipag Tablets

1,400 mcg

60 Tablets

Rx only

NDC 70771-1800-6

Selexipag Tablets

1,600 mcg

60 Tablets

Rx only

NDC 70771-1801-7

TITRATION PACK

Selexipag Tablets

200 mcg

140 Tablets

Rx only

Selexipag Tablets

800 mcg

60 Tablets

Rx only